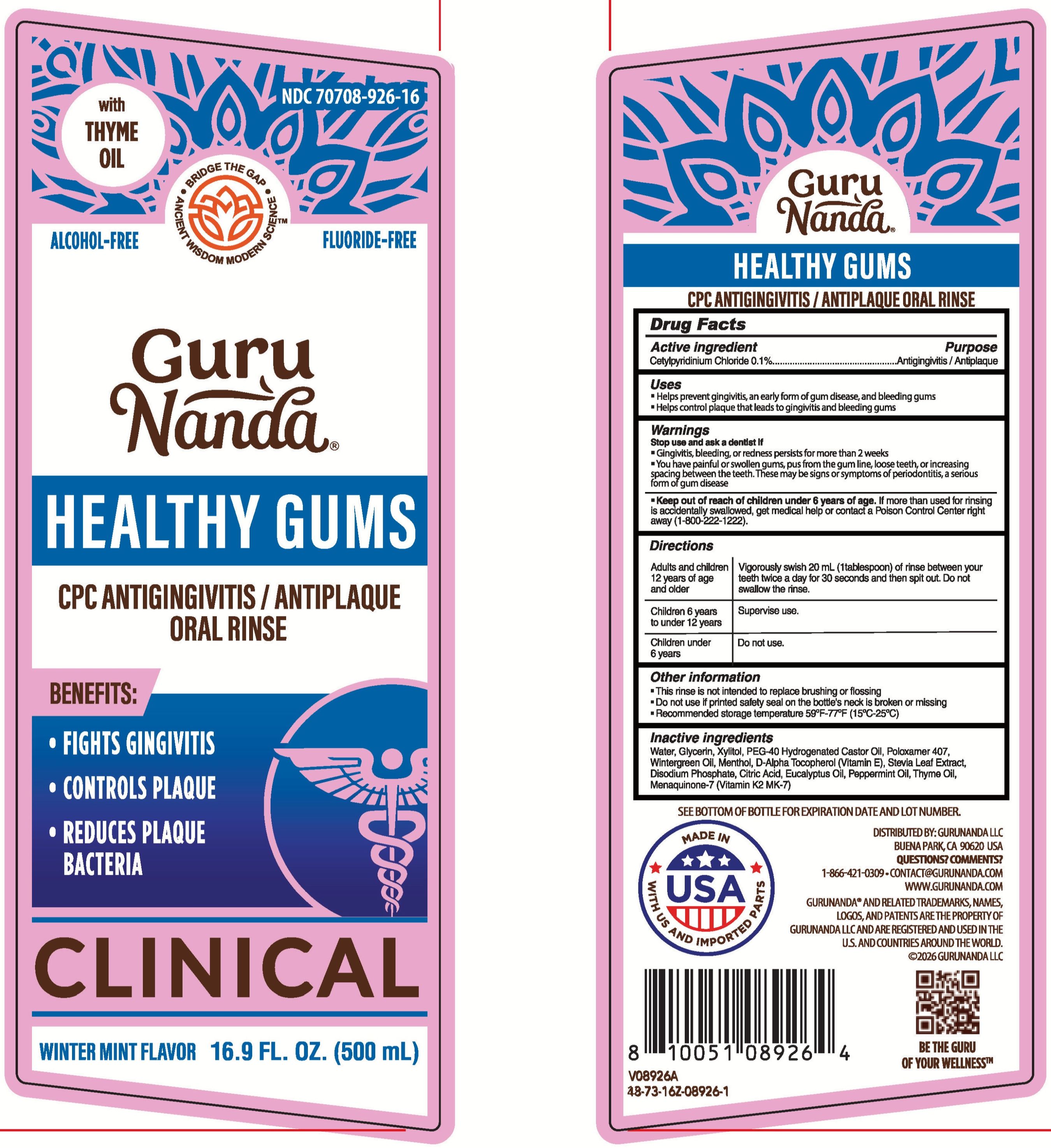 DRUG LABEL: GuruNanda Healthy Gums
NDC: 70708-926 | Form: MOUTHWASH
Manufacturer: GURUNANDA, LLC
Category: otc | Type: HUMAN OTC DRUG LABEL
Date: 20260119

ACTIVE INGREDIENTS: CETYLPYRIDINIUM CHLORIDE 1 mg/1 mL
INACTIVE INGREDIENTS: THYME OIL; MENAQUINONE-7; STEVIA LEAF; DISODIUM PHOSPHATE; MENTHOL; PEG-40 HYDROGENATED CASTOR OIL; EUCALYPTUS OIL; POLOXAMER 407; PEPPERMINT OIL; CITRIC ACID; XYLITOL; METHYL SALICYLATE; .ALPHA.-TOCOPHEROL, D-; WATER

GN Healthy Gums Mouthwash

Active ingredient

Cetylpyridinium Chloride 0.1%

Purpose

Antigingivitis/Antiplaque

Uses

- Helps prevent gingivitis, an early form of gum disease, and bleeding gums
- Helps control plaque that leads to gingivitis and bleeding gums

Warnings

Stop use and ask a dentist if

- Gingivitis, bleeding, or redness persists for more than 2 weeks
- You have painful or swollen gums, pus from the gum line, loose teeth, or icnreasing spacing between the teeth. These may be signs or symptoms of periodontitis, a serious form of gum disease

Keep out of reach of children under 6 years of age.

If more than used for rinsing is accidentally swallowed, get medical help or contact a Poison Control Center right away (1-800-222-1222).

Directions

Adults and children 12 years of age and older: Vigorougly swish 20 mL (1 tablespoon) of rinse between your teeth twice a day for 30 seconds and then spit out. Do not swallow the rinse.

Children 6 years to under 12 years: Supervise use.

Children under 6 years: Do not use.

Other information

- This rinse is not intended to replace brushing or flossing
- Do not use if printed safety seal on the bottle's neck is broken or missing
- Recommended storage temperature 59°F-77°F (15°C-25°C)

Inactive ingredients

Water, Glycerin, Xylitol, PEG-40 Hydrogenated Castor Oil, Poloxamer 407, Wintergreen Oil, Menthol, D-Alpha Tocopherol (Vitamin E), Stevia Leaf Extract, Disodium Phosphate, Citric Acid, Eucalyptus Oil, Peppermint Oil, Thyme Oil, Menaquinone-7 (Vitamin K2 MK-7)